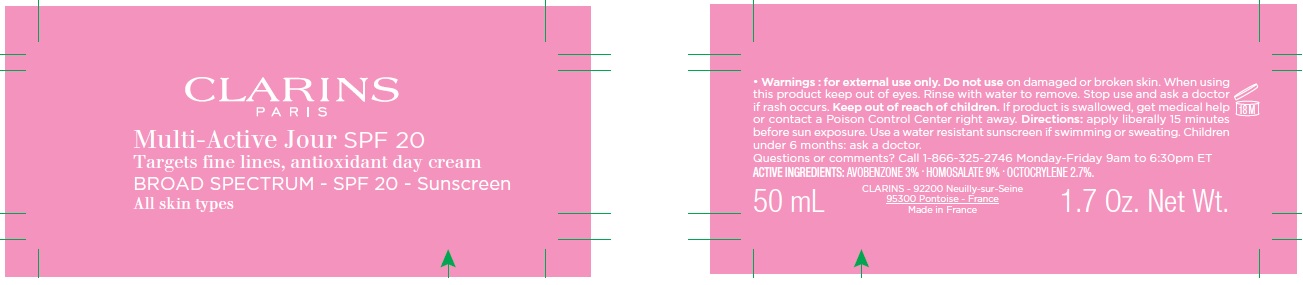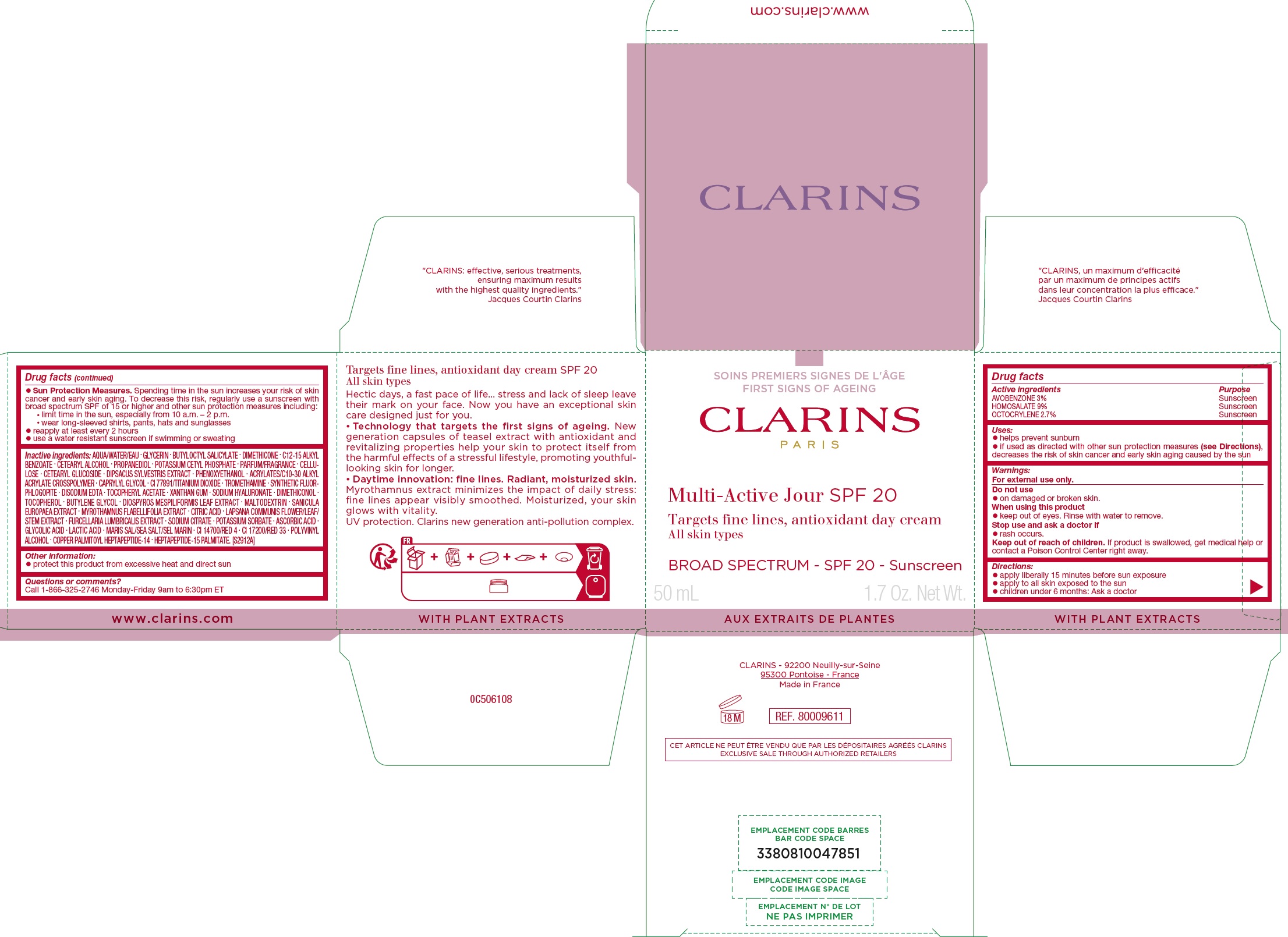 DRUG LABEL: Multi-Active Jour SPF 20 Broad Spectrum Sunscreen
NDC: 58668-9611 | Form: CREAM
Manufacturer: Laboratoires Clarins
Category: otc | Type: HUMAN OTC DRUG LABEL
Date: 20231208

ACTIVE INGREDIENTS: AVOBENZONE 30 mg/1 mL; HOMOSALATE 90 mg/1 mL; OCTOCRYLENE 27 mg/1 mL
INACTIVE INGREDIENTS: XANTHAN GUM; HYALURONATE SODIUM; TOCOPHEROL; BUTYLENE GLYCOL; DIOSPYROS MESPILIFORMIS LEAF; MALTODEXTRIN; CITRIC ACID MONOHYDRATE; LAPSANA COMMUNIS FLOWERING TOP; FURCELLERAN; SODIUM CITRATE; POTASSIUM SORBATE; ASCORBIC ACID; GLYCOLIC ACID; LACTIC ACID; FD&C RED NO. 4; D&C RED NO. 33; POLYVINYL ALCOHOL, UNSPECIFIED; WATER; GLYCERIN; BUTYLOCTYL SALICYLATE; DIMETHICONE; ALKYL (C12-15) BENZOATE; CETOSTEARYL ALCOHOL; PROPANEDIOL; POTASSIUM CETYL PHOSPHATE; POWDERED CELLULOSE; CETEARYL GLUCOSIDE; PHENOXYETHANOL; CAPRYLYL GLYCOL; TITANIUM DIOXIDE; TROMETHAMINE; EDETATE DISODIUM ANHYDROUS; .ALPHA.-TOCOPHEROL ACETATE

Multi-Active Jour SPF 20 Broad Spectrum Sunscreen

Active ingredients

AVOBENZONE 3%

HOMOSALTE 9%

OCTOCRYLENE 2.7%

Purpose

Sunscreen

Uses:

• helps prevent sunburn • if used as directed with other sun protection measures (see Directions), decreases the risk of skin cancer and early skin aging caused by the sun

Warnings:

For external use only.

Do not use

- on damaged or broken skin.

When using this product

- keep out of eyes. Rinse with water to remove.

Stop use and ask a doctor if

- rash occurs.

Keep out of reach of children.

If product is swallowed, get medical help or contact a Poison Control Center right away.

Directions:

• apply liberally 15 minutes before sun exposure • apply to all skin exposed to the sun • children under 6 months: Ask a doctor • Sun Protection Measures. Spending time in the sun increases your risk of skin cancer and early skin aging. To decrease this risk, regularly use a sunscreen with broad spectrum SPF of 15 or higher and other sun protection measures including: • limit time in the sun, especially from 10 a.m. – 2 p.m. • wear long-sleeved shirts, pants, hats and sunglasses • reapply at least every 2 hours • use a water resistant sunscreen if swimming or sweating

Inactive ingredients

AQUA/WATER/EAU . GLYCERIN . BUTYLOCTYL SALICYLATE . DIMETHICONE . C12-15 ALKYL BENZOATE . CETEARYL ALCOHOL . PROPANEDIOL . POTASSIUM CETYL PHOSPHATE . PARFUM/FRAGRANCE . CELLULOSE . CETEARYL GLUCOSIDE . DIPSACUS SYLVESTRIS EXTRACT . PHENOXYETHANOL . ACRYLATES/C10-30 ALKYL ACRYLATE CROSSPOLYMER . CAPRYLYL GLYCOL . CI 77891/TITANIUM DIOXIDE . TROMETHAMINE . SYNTHETIC FLUORPHLOGOPITE . DISODIUM EDTA . TOCOPHERYL ACETATE . XANTHAN GUM . SODIUM HYALURONATE . DIMETHICONOL . TOCOPHEROL . BUTYLENE GLYCOL . DIOSPYROS MESPILIFORMIS LEAF EXTRACT . MALTODEXTRIN . SANICULA EUROPAEA EXTRACT . MYROTHAMNUS FLABELLIFOLIA EXTRACT . CITRIC ACID . LAPSANA COMMUNIS FLOWER/LEAF/ STEM EXTRACT . FURCELLARIA LUMBRICALIS EXTRACT . SODIUM CITRATE . POTASSIUM SORBATE . ASCORBIC ACID . GLYCOLIC ACID . LACTIC ACID . MARIS SAL/SEA SALT/SEL MARIN . CI 14700/RED 4 . CI 17200/RED 33 . POLYVINYL ALCOHOL . COPPER PALMITOYL HEPTAPEPTIDE-14 . HEPTAPEPTIDE-15 PALMITATE. [S2912A]

Other information:

• protect this product from excessive heat and direct sun

Questions or comments?

Call 1-866-325-2746 Monday-Friday 9am to 6:30pm ET